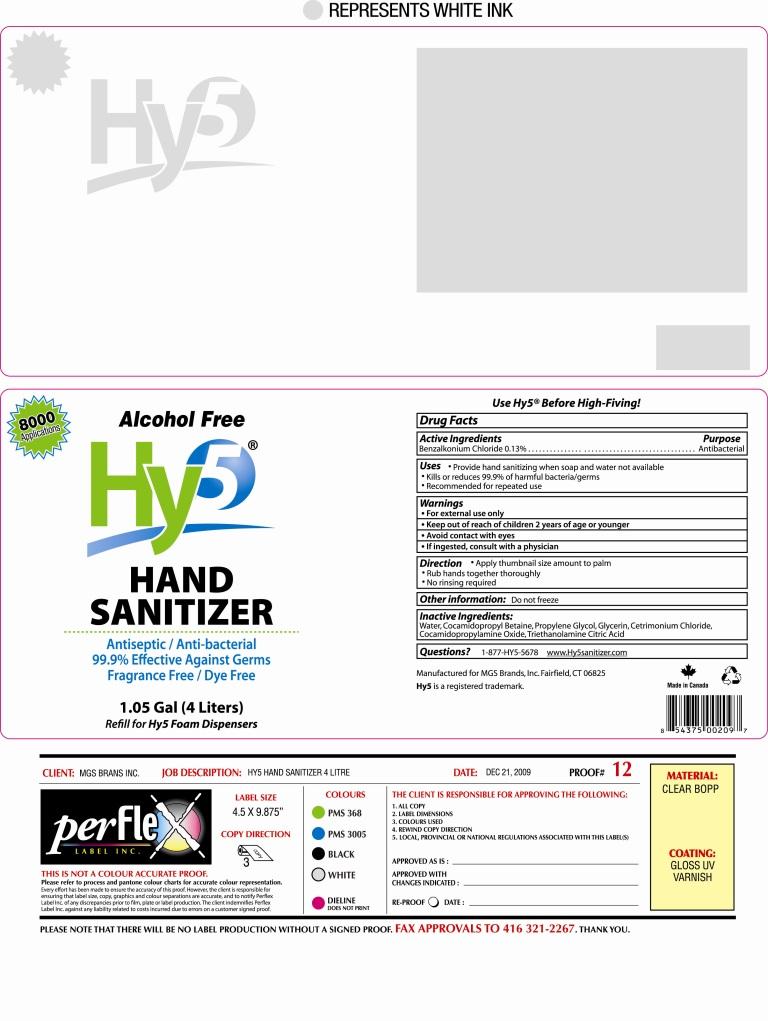 DRUG LABEL: Hy5 
NDC: 50136-555 | Form: LIQUID
Manufacturer: MGS Brands, Inc.
Category: otc | Type: HUMAN OTC DRUG LABEL
Date: 20100109

ACTIVE INGREDIENTS: Benzalkonium Chloride 0.13 L/100 L
INACTIVE INGREDIENTS: Cetrimonium Chloride; Citric Acid Monohydrate; COCAMIDOPROPYL BETAINE; Glycerin; PROPYLENE GLYCOL; TROLAMINE; Water

Hy5 Alcohol Free Hand Sanitizer

ACTIVE INGREDIENT

Benzalkonium Chloride 0.13%

PURPOSE

Antibacterial

PURPOSE

- Provide hand sanitizing when soap and water not available
- Kills or reduces 99.9% of harmful bacteria/germs
- Recommended for repeated use

WARNINGS

- For external use only
- Keep out of reach of children 2 years of age or younger
- Avoid contact with eyes
- If ingested, consult with a physician

DOSAGE AND ADMINISTRATION

- Apply thumbnail size amount to palm
- Rub hands together thoroughly
- No rinsing required

Do not freeze

INACTIVE INGREDIENT

Water, Cocamidopropyl Betaine, Propylene Glycol, Glycerine, Cetrimonium Chloride, Cocamidopropylamine Oxide, Triethanolamine, Citric Acid

QUESTIONS

1-877-Hy5-5678 www.Hy5sanitizer.com

Image of 4L Jug Label